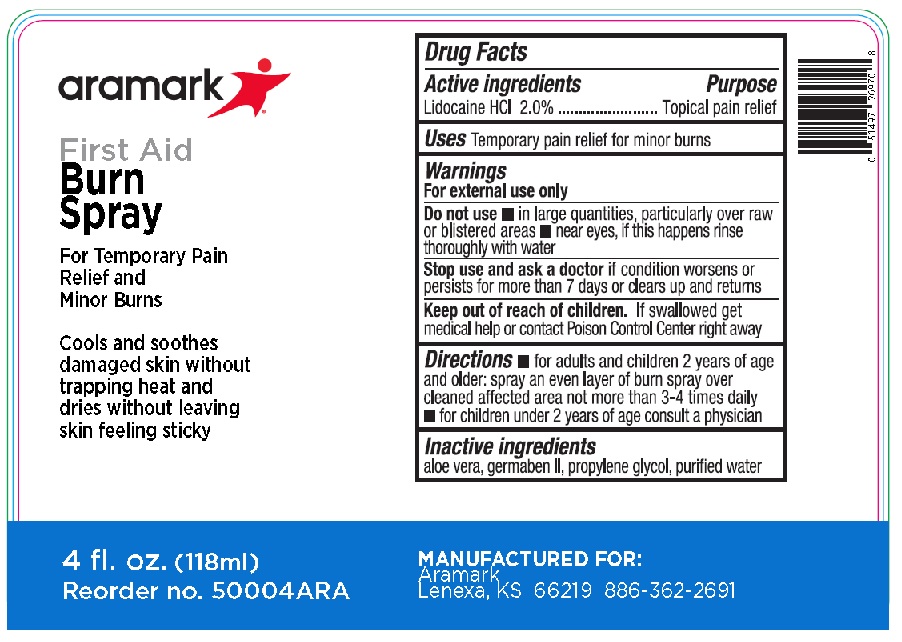 DRUG LABEL: Aramark Burn
NDC: 81238-5100 | Form: SPRAY
Manufacturer: Western First Aid Safety DBA Aramark
Category: otc | Type: HUMAN OTC DRUG LABEL
Date: 20210628

ACTIVE INGREDIENTS: LIDOCAINE HYDROCHLORIDE 20 mg/1 mL
INACTIVE INGREDIENTS: ALOE VERA LEAF; DIAZOLIDINYL UREA; PROPYLENE GLYCOL; WATER

Aramark Burn Spray

Drug Facts

Active ingredients

Lidocaine HCl 2.0%

Purpose

Topical pain relief

Uses

Temporary pain relief for minor burns

Warnings

For external use only

Do not use • in large quantities, particularly over raw

or blistered areas • near eyes, if this happens rinse

thoroughly with water

Stop use and ask a doctor if condition worsens or

continues for more than 7 days or clears up and returns

Keep out of reach of children. If swallowed get

medical help or contact Poison Control Center right away

DOSAGE AND ADMINISTRATION

Directions• for adults and children 2 years of age

and older: spray an even layer of burn spray over

cleaned affected area not more than 3-4 times daily
• for children under 2 years of age consult a physician

Inactive ingredients

aloe vera, germaben II, propylene glycol, purified water

PRINCIPAL DISPLAY PANEL – 3 oz. bottle

aramark

First Aid
Burn Spray

For Temporary Pain
Relief and
Minor Burns

4 fl. oz. (118 mL)

Reorder no. 50004ARA

MANUFACTURED FOR:
Aramark
Lenexa, KS 66219 886-362-2691

res